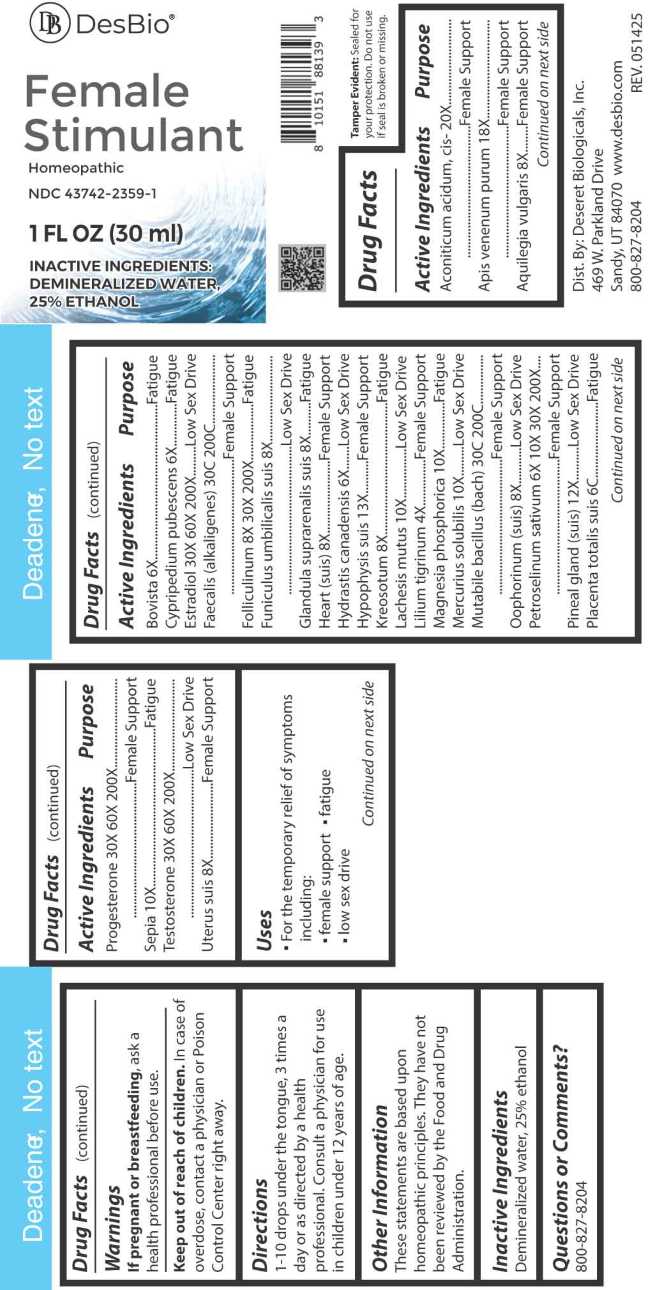 DRUG LABEL: Female Stimulant
NDC: 43742-2359 | Form: LIQUID
Manufacturer: Deseret Biologicals, Inc.
Category: homeopathic | Type: HUMAN OTC DRUG LABEL
Date: 20260219
DEA Schedule: CIII

ACTIVE INGREDIENTS: ACONITIC ACID, (Z)- 20 [hp_X]/1 mL; APIS MELLIFERA VENOM 18 [hp_X]/1 mL; AQUILEGIA VULGARIS 8 [hp_X]/1 mL; LYCOPERDON UTRIFORME FRUITING BODY 6 [hp_X]/1 mL; CYPRIPEDIUM PARVIFLORUM VAR. PUBESCENS ROOT 6 [hp_X]/1 mL; ESTRADIOL 30 [hp_X]/1 mL; ALCALIGENES FAECALIS 30 [hp_C]/1 mL; ESTRONE 8 [hp_X]/1 mL; SUS SCROFA UMBILICAL CORD 8 [hp_X]/1 mL; SUS SCROFA ADRENAL GLAND 8 [hp_X]/1 mL; PORK HEART 8 [hp_X]/1 mL; GOLDENSEAL 6 [hp_X]/1 mL; SUS SCROFA PITUITARY GLAND 13 [hp_X]/1 mL; WOOD CREOSOTE 8 [hp_X]/1 mL; LACHESIS MUTA VENOM 10 [hp_X]/1 mL; LILIUM LANCIFOLIUM WHOLE FLOWERING 4 [hp_X]/1 mL; MAGNESIUM PHOSPHATE, DIBASIC TRIHYDRATE 10 [hp_X]/1 mL; MERCURIUS SOLUBILIS 10 [hp_X]/1 mL; ESCHERICHIA COLI 30 [hp_C]/1 mL; SUS SCROFA OVARY 8 [hp_X]/1 mL; PETROSELINUM CRISPUM WHOLE 6 [hp_X]/1 mL; SUS SCROFA PINEAL GLAND 12 [hp_X]/1 mL; SUS SCROFA PLACENTA 6 [hp_C]/1 mL; PROGESTERONE 30 [hp_X]/1 mL; SEPIA OFFICINALIS JUICE 10 [hp_X]/1 mL; TESTOSTERONE 30 [hp_X]/1 mL; SUS SCROFA UTERUS 8 [hp_X]/1 mL
INACTIVE INGREDIENTS: WATER; ALCOHOL

DRUG FACTS:

ACTIVE INGREDIENTS:

Aconiticum Acidum, Cis- 20X, Apis Venenum Purum 18X, Aquilegia Vulgaris 8X, Bovista 6X, Cypripedium Pubescens 6X, Estradiol 30X, 60X, 200X, Faecalis (Alkaligenes) 30C, 200C, Folliculinum 8X, 30X, 200X, Funiculus Umbilicalis Suis 8X, Glandula Suprarenalis Suis 8X, Heart (Suis) 8X, Hydrastis Canadensis 6X, Hypophysis Suis 13X, Kreosotum 8X, Lachesis Mutus 10X, Lilium Tigrinum 4X, Magnesia Phosphorica 10X, Mercurius Solubilis 10X, Mutabile Bacillus (Bach) 30C, 200C, Oophorinum (Suis) 8X, Petroselinum Sativum 6X, 10X, 30X, 200X, Pineal Gland (Suis) 12X, Placenta Totalis Suis 6C, Progesterone 30X, 60X, 200X, Sepia 10X, Testosterone 30X, 60X, 200X, Uterus (Suis) 8X.

PURPOSE:

Aconiticum Acidum, Cis- Female Support, Apis Venenum Purum – Female Support, Aquilegia Vulgaris – Female Support, Bovista - Fatigue, Cypripedium Pubescens - Fatigue, Estradiol – Low Sex Drive, Faecalis (Alkaligenes) – Female Support, Folliculinum - Fatigue, Funiculus Umbilicalis Suis – Low Sex Drive, Glandula Suprarenalis Suis - Fatigue, Heart (Suis) – Female Support, Hydrastis Canadensis – Low Sex Drive, Hypophysis Suis – Female Support, Kreosotum - Fatigue, Lachesis Mutus – Low Sex Drive, Lilium Tigrinum – Female Support, Magnesia Phosphorica - Fatigue, Mercurius Solubilis – Low Sex Drive, Mutabile Bacillus (Bach) – Female Support, Oophorinum (Suis) – Low Sex Drive, Petroselinum Sativum – Female Support, Pineal Gland (Suis) – Low Sex Drive, Placenta Totalis Suis - Fatigue, Progesterone – Female Support, Sepia - Fatigue, Testosterone – Low Sex Drive, Uterus (Suis) – Female Support

USES:

• For the temporary relief of symptoms including:

• female support • fatigue • low sex drive

These statements are based upon homeopathic principles. They have not been reviewed by the Food and Drug Administration.

WARNINGS:

If pregnant or breastfeeding, ask a health professional before use.

Keep out of reach of children. In case of overdose, contact a physician or Poison Control Center right away.

Tamper Evident: Sealed for your protection. Do not use if seal is broken or missing.

KEEP OUT OF REACH OF CHILDREN:

In case of overdose, contact a physician or Poison Control Center right away.

DIRECTIONS:

1-10 drops under the tongue, 3 times a day or as directed by a health professional. Consult a physician for use in children under 12 years of age.

INACTIVE INGREDIENTS:

Demineralized water, 25% ethanol

QUESTIONS:

Dist. By: Deseret Biologicals, Inc.
469 W. Parkland Drive
Sandy, UT 84070

www.desbio.com

800-827-8204

PACKAGE LABEL DISPLAY:

DesBio

Female Stimulant

Homeopathic

NDC 43742-2359-1

1 FL OZ (30ml)